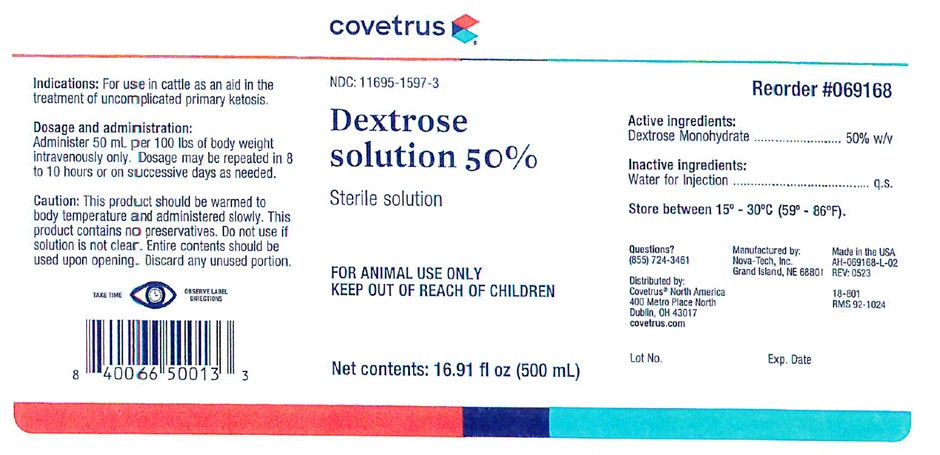 DRUG LABEL: Dextrose
NDC: 11695-1597 | Form: INJECTION, SOLUTION
Manufacturer: Covetrus
Category: animal | Type: OTC ANIMAL DRUG LABEL
Date: 20231227

ACTIVE INGREDIENTS: DEXTROSE MONOHYDRATE 50 g/100 mL

Dextrose Solution 50%

Dosage And Administration:

Administer 50 mL per 100 lbs of body weight intravenously only. Dosage may be repeated in 8 to 10 hours or on successive days as needed.

Caution:

This product should be warmed to body temperature and administered slowly. This product contains no preservative. Do not use if solution is not clear. Entire contents should be used upon opening. Discard any unused portion.

GENERAL PRECAUTIONS

FOR ANIMAL USE ONLY
KEEP OUT OF REACH OF CHILDREN

Active Ingredients:

Dextrose Monohydrate ..........................50 % w/v

Inactive Ingredients:

Water for Injection .......................... q.s.

STORAGE AND HANDLING

Store between 15°C and 30°C (59°F-86°F).

GENERAL PRECAUTIONS

TAKE TIME OBSERVE LABEL DIRECTIONS

INFORMATION FOR OWNERS/CAREGIVERS

NDC: 11695-1597-3

18-801
RMS 92-1024

Volume: 16.907 (500 mL)

Questions? (855) 724-3461

Reorder #069168

Manufactured by:
Nova-Tech, Inc.
Grand Island, NE 68801

Distributed by:
Covetrus North America

400 Metro Place North

Dublin, OH 43017

covetrus.com

Made in the USA

AH-069168-L-02
Rev: 0523

Lot No. Exp. Date

Indications:

For use in cattle as an aid in the treatment of uncomplicated primary ketosis.